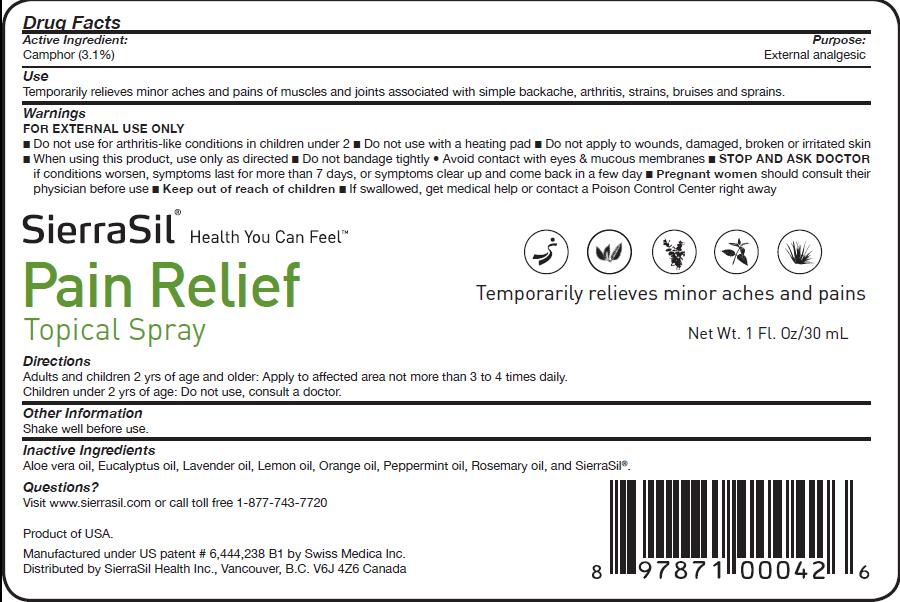 DRUG LABEL: SierraSil
NDC: 50802-001 | Form: SPRAY
Manufacturer: Sierra Mountain Minerals Inc. d/b/a Sierra Sil Health Inc.
Category: otc | Type: HUMAN OTC DRUG LABEL
Date: 20100525

ACTIVE INGREDIENTS: CAMPHOR OIL 1 mL/30 mL

ACTIVE INGREDIENT

Camphor (3.1%)

PURPOSE

External analgesic

Uses:

Temporarily relieves minor aches and pains of muscles and joints associated with simple backache, arthritis, strains, bruises and sprains.

WARNINGS

FOR EXTERNAL USE ONLY

Do not use for arthritis-like conditions in children under 2

Do not use with a heating pad

Do not apply to wounds, damaged, broken or irritated skin

When using this product, use only as directed

Do not bandage tightly

Avoid contact with eyes and mucous membranes

ASK DOCTOR

Stop and ask doctor if conditions worsens, symptoms last for more than 7 days, or symptoms clear up and come back in a few days

PREGNANCY OR BREAST FEEDING

Pregnant women should consult their physician before use

Keep out of reach of children

If swallowed, get medical help or contact a Poison Control Center right away

DOSAGE AND ADMINISTRATION

Adults and children 2 yrs of age and older: Apply to affected area not more than 3 to 4 times daily.

Children under 2 yrs of age: Do not use, consult a doctor.

INACTIVE INGREDIENT

Aloe vera oil, Eucalyptus oil, Lavender oil, Lemon oil, Orange oil, Peppermint oil, Rosemary oil, and SierraSil

Questions?

Visit www.sierrasil.com or call toll free 1-877-743-7720

STORAGE AND HANDLING

Shake well before use

PACKAGE LABEL

Sierra Sil

Pain Relief

Health You Can Feel

Temporarily relieves minor aches and pains

Product of USA
Manufactured under US patent number 6,444,238 B1 by Swiss Medica Inc.
Distributed by SierraSil Health Inc., Vancouver, B.C. V6J 4Z6 Canada